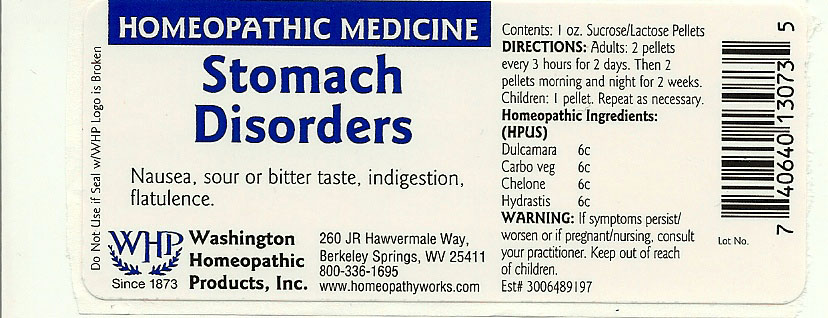 DRUG LABEL: Stomach Disorders
NDC: 68428-004 | Form: PELLET
Manufacturer: Washington Homeopathic Products
Category: homeopathic | Type: HUMAN OTC DRUG LABEL
Date: 20191223

ACTIVE INGREDIENTS: SOLANUM DULCAMARA TOP 6 [hp_C]/28 g; ACTIVATED CHARCOAL 6 [hp_C]/28 g; CHELONE GLABRA 6 [hp_C]/28 g; GOLDENSEAL 6 [hp_C]/28 g
INACTIVE INGREDIENTS: SUCROSE; LACTOSE

DRUG FACTS

ACTIVE INGREDIENTS

DULCAMARA 6C

CARBO VEG 6C

CHELONE 6C

HYDRASTIS 6C

USES

To relieve the symptoms of nausea, sour or bitter taste, indigestion, flatulence.

KEEP OUT OF REACH OF CHILDREN

Keep this and all medicines out of reach of children.

INDICATIONS

DULCAMARA colds

CARBO VEG Exhaustion

CHELONE Worms

HYDRASTIS Sinuses

STOP USE AND ASK DOCTOR

If symptoms persist/worsen or if pregnant/nursing, stop use and consult your practitioner.

DIRECTIONS

Adults 2 pellets every 3 hours for 2 days. Then 2 pellets morning and night for 2 weeks.

Children: 1 pellet. Repeat as necessary.

INACTIVE INGREDIENTS

Sucrose/Lactose

PRINCIPAL DISPLAY PANEL

Enter section text here